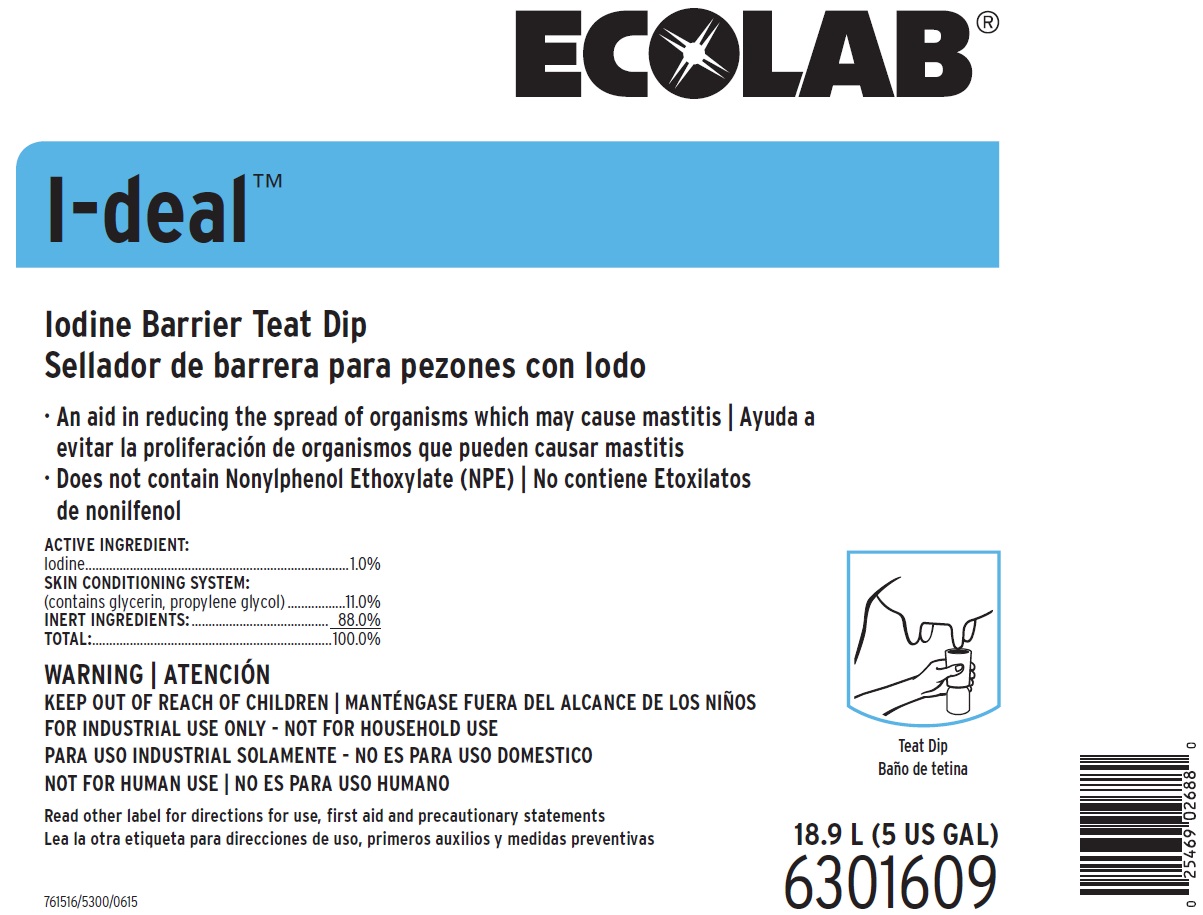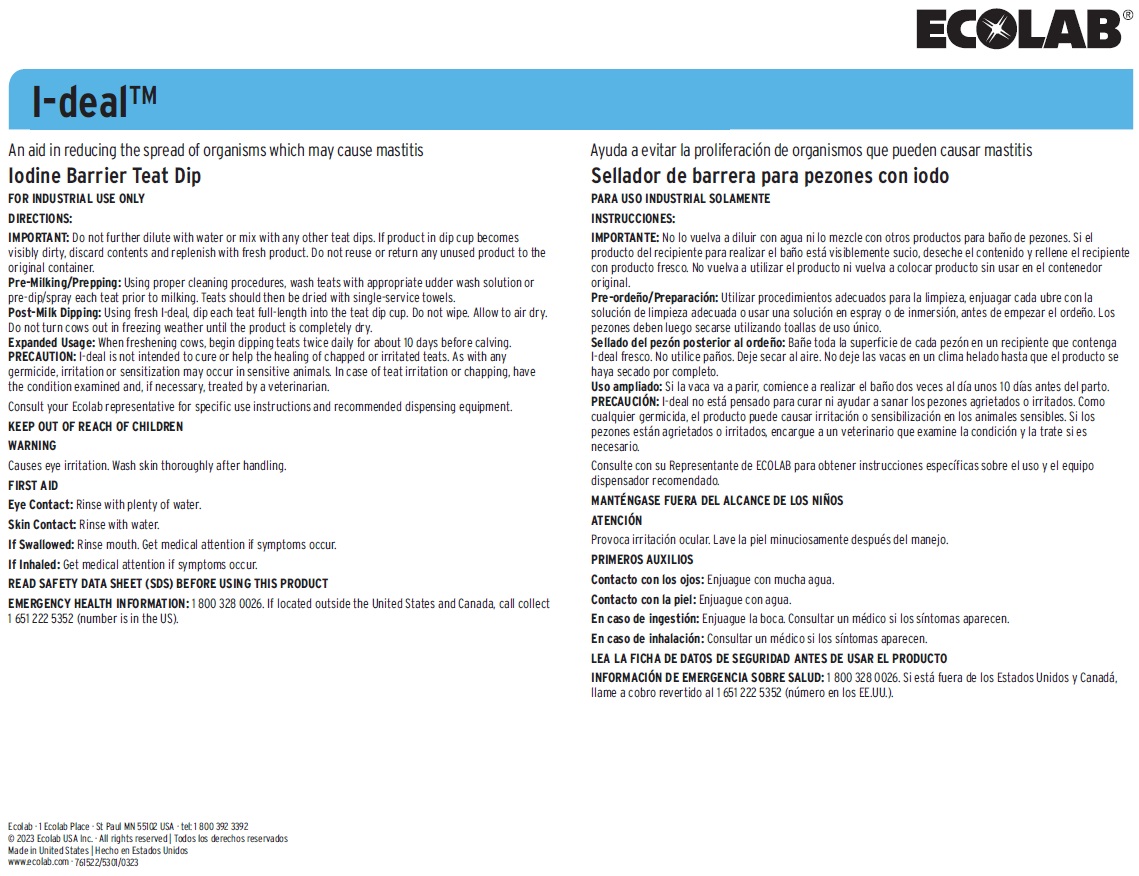 DRUG LABEL: I-deal
NDC: 47593-550 | Form: SOLUTION
Manufacturer: Ecolab Inc. 
Category: animal | Type: OTC ANIMAL DRUG LABEL
Date: 20251005

ACTIVE INGREDIENTS: IODINE 10 mg/1 mL
INACTIVE INGREDIENTS: WATER; PROPYLENE GLYCOL; GLYCERIN

WARNING | ATENCIÓN

KEEP OUT OF REACH OF CHILDREN |
MANTÉNGASE FUERA DEL ALCANCE DE LOS NIÑOS
FOR INDUSTRIAL USE ONLY - NOT FOR HOUSEHOLD USE
PARA USO INDUSTRIAL SOLAMENTE - NO ES PARA USO DOMESTICO
NOT FOR HUMAN USE | NO ES PARA USO HUMANO

Read other label for directions for use, first aid and precautionary statements
Lea la otra etiqueta para direcciones de uso, primeros auxilios y medidas preventivas

VETERINARY INDICATIONS

Iodine Barrier Teat Dip

FOR INDUSTRIAL USE ONLY

DIRECTIONS:

IMPORTANT: Do not further dilute with water or mix with any other teat dips. If product in dip cup becomes visibly dirty, discard
contents and replenish with fresh product. Do not reuse or return any unused product to the original container.
Pre-Milking/Prepping: Using proper cleaning procedures, wash teats with appropriate udder wash solution or pre-dip/spray each teat
prior to milking. Teats should then be dried with single-service towels.
Post-Milk Dipping: Using fresh I-deal, dip each teat full-length into the teat dip cup. Do not wipe. Allow to air dry. Do not turn cows
out in freezing weather until the product is completely dry.
Expanded Usage: When freshening cows, begin dipping teats twice daily for about 10 days before calving.
PRECAUTION: I-deal is not intended to cure or help the healing of chapped or irritated teats. As with any germicide, irritation or
sensitization may occur in sensitive animals. In case of teat irritation or chapping, have the condition examined and, if necessary,
treated by a veterinarian.

Consult your Ecolab representative for specific use instructions and recommended dispensing equipment.

KEEP OUT OF REACH OF CHILDREN

WARNING

Causes eye irritation. Wash skin thoroughly after handling.

FIRST AID

Eye Contact: Rinse with plenty of water.

Skin Contact: Rinse with water.

If Swallowed: Rinse mouth. Get medical attention if symptoms occur.

If Inhaled: Get medical attention if symptoms occur.

READ SAFETY DATA SHEET (SDS) BEFORE USING THIS PRODUCT

EMERGENCY HEALTH INFORMATION: 1 800 328 0026. If located outside the United States and Canada, call collect 1 651 222 5352 (number is in the US).

Principal Display Panel and Representative Label

ECOLAB®

I-deal™

Iodine Barrier Teat Dip

Sellador de barrera para pezones con Iodo

- An aid in reducing the spread of organisms which may cause mastitis | Ayuda a evitar la proliferación de organismos que pueden causar mastitis
- Does not contain Nonylphenol Ethoxylate (NPE) | No contiene Etoxilatos de nonilfenol

ACTIVE INGREDIENT: Iodine.................................................................1.0%

SKIN CONDITIONING SYSTEM:(contains glycerin, propylene glycol)....................11.0%

INERT INGREDIENTS:.................................... 88.0%

TOTAL:............................................................100.0%

WARNING | ATENCIÓN

KEEP OUT OF REACH OF CHILDREN | MANTÉNGASE FUERA DEL ALCANCE DE LOS NIÑOS

FOR INDUSTRIAL USE ONLY - NOT FOR HOUSEHOLD USE

PARA USO INDUSTRIAL SOLAMENTE - NO ES PARA USO DOMESTICO

NOT FOR HUMAN USE | NO ES PARA USO HUMANO

Read other label for directions for use, first aid and precautionary statements

Lea la otra etiqueta para direcciones de uso, primeros auxilios y medidas preventivas

18.9L (5 US GAL)

6301609

761516/5300/0615